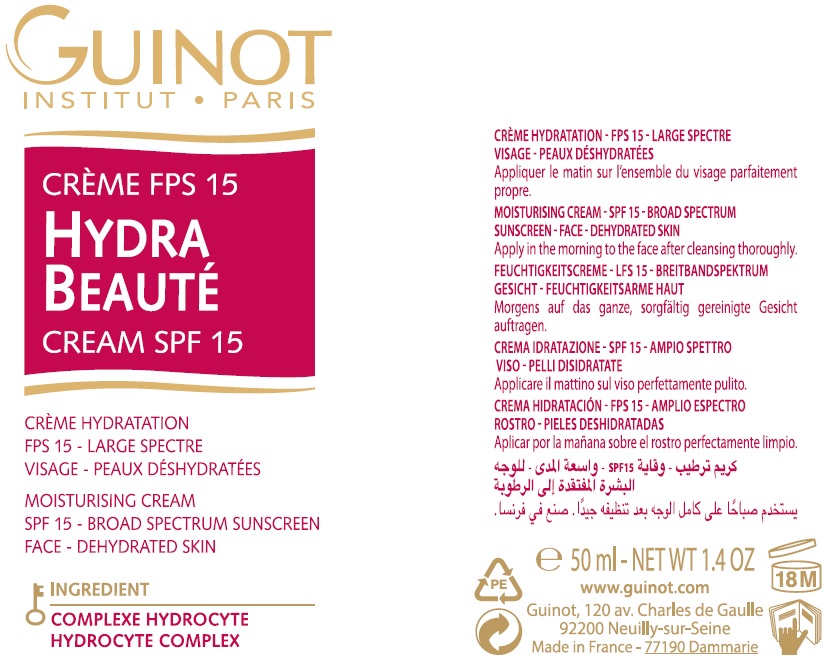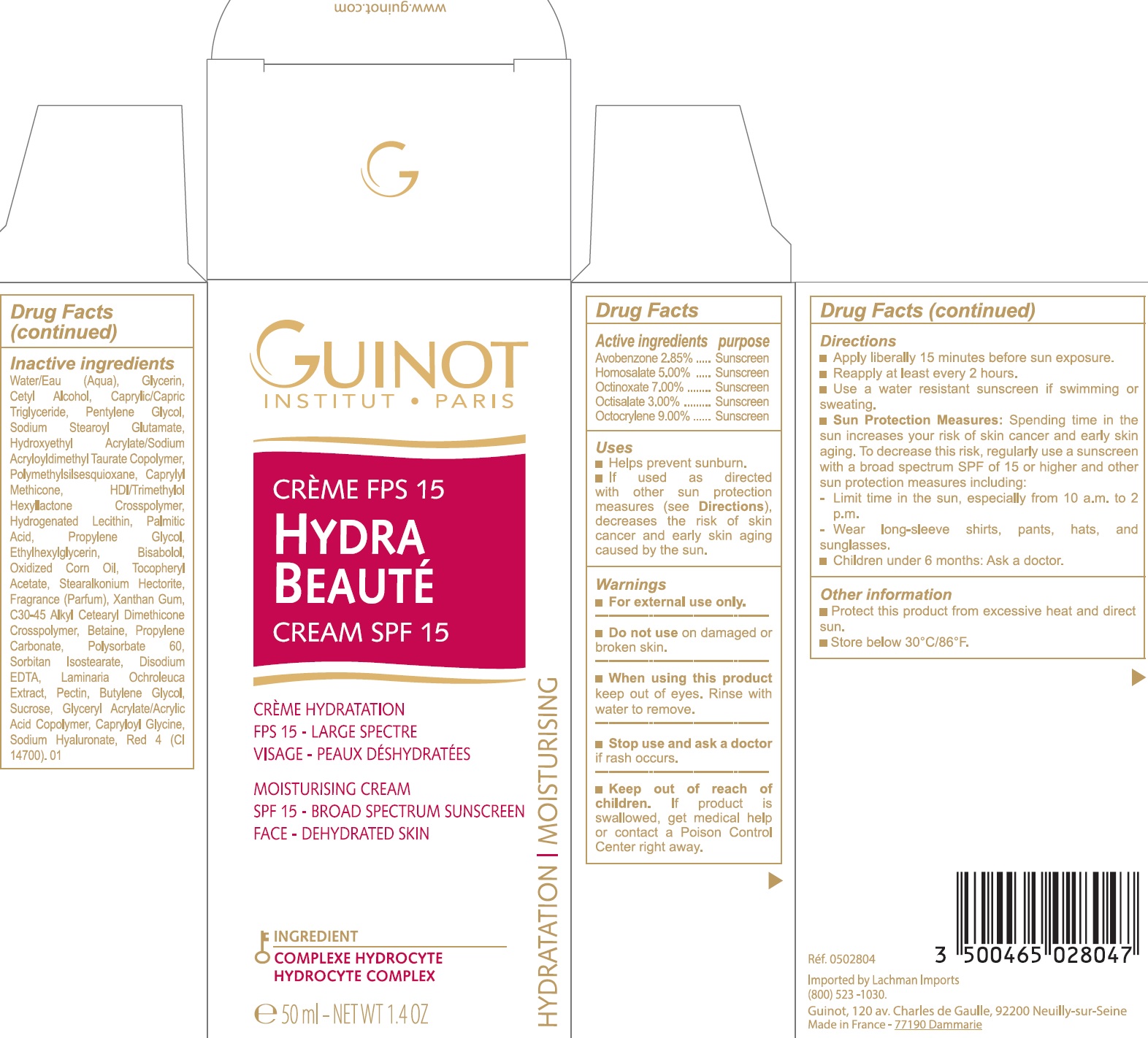 DRUG LABEL: HYDRA BEAUTE SPF 15
NDC: 54181-009 | Form: CREAM
Manufacturer: Guinot
Category: otc | Type: HUMAN OTC DRUG LABEL
Date: 20260129

ACTIVE INGREDIENTS: AVOBENZONE 28.5 mg/1 mL; HOMOSALATE 50 mg/1 mL; OCTINOXATE 70 mg/1 mL; OCTISALATE 30 mg/1 mL; OCTOCRYLENE 90 mg/1 mL
INACTIVE INGREDIENTS: SODIUM STEAROYL GLUTAMATE; HYDROXYETHYL ACRYLATE/SODIUM ACRYLOYLDIMETHYL TAURATE COPOLYMER (100000 MPA.S AT 1.5%); POLYMETHYLSILSESQUIOXANE (4.5 MICRONS); CAPRYLYL TRISILOXANE; HEXAMETHYLENE DIISOCYANATE/TRIMETHYLOL HEXYLLACTONE CROSSPOLYMER; HYDROGENATED SOYBEAN LECITHIN; PALMITIC ACID; PROPYLENE GLYCOL; ETHYLHEXYLGLYCERIN; LEVOMENOL; STEARALKONIUM HECTORITE; XANTHAN GUM; BETAINE; PROPYLENE CARBONATE; POLYSORBATE 60; SORBITAN ISOSTEARATE; EDETATE DISODIUM ANHYDROUS; PECTIN; BUTYLENE GLYCOL; SUCROSE; CAPRYLOYL GLYCINE; HYALURONATE SODIUM; FD&C RED NO. 4; WATER; GLYCERIN; CETYL ALCOHOL; MEDIUM-CHAIN TRIGLYCERIDES; PENTYLENE GLYCOL

HYDRA BEAUTE CREAM SPF 15

Active ingredients

Avobenzone 2.85%

Homosalate 5.00%

Octinoxate 7.00%

Octisalate 3.00%

Octocrylene 9.00%

Purpose

Sunscreen

Uses

- Helps prevent sunburn.
- If used as directed with other sun protection measures (see), decreases the risk of skin cancer and early skin aging caused by the sun. Directions

Warnings

- For external use only.

Do not use

on damaged or broken skin.

When using this product

keep out of eyes. Rinse with water to remove.

Stop use and ask a doctor

if rash occurs.

Keep out of reach of children.

If product is swallowed, get medical help or contact a Poison Control Center right away.

Directions

- Apply liberally 15 minutes before sun exposure.
- Reapply at least every 2 hours.
- Use a water resistant sunscreen if swimming or sweating.
- Spending time in the sun increases your risk of skin cancer and early skin aging. To decrease this risk, regularly use a sunscreen with a broad spectrum SPF of 15 or higher and other sun protection measures including: Sun Protection Measures:

- Children under 6 months: Ask a doctor.

- Limit time in the sun, especially from 10 a.m. to 2 p.m.

- Wear long-sleeve shirts, pants hats, and sunglasses.

Other information

- Protect this product from excessive heat and direct sun.
- Store below 30°C/86°F.

Inactive ingredients

Water/Eau (Aqua), Glycerin, Cetyl Alcohol, Caprylic/Capric Triglyceride, Pentylene Glycol, Sodium Stearoyl Glutamate, Hydroxyethyl Acrylate/Sodium Acryloyldimethyl Taurate Copolymer, Polymethylsilsesquioxane, Caprylyl Methicone, HDI/Trimethylol Hexyllactone Crosspolymer, Hydrogenated Lecithin, Palmitic Acid, Propylene Glycol, Ethylhexylglycerin, Bisabolol, Oxidized Corn Oil, Tocopheryl Acetate, Stearalkonium Hectorite, Fragrance (Parfum), Xanthan Gum, C30-45 Alkyl Cetearyl Diemthicone Crossspolymer, Betaine, Propylene Carbonate, Polysorbate 60, Sorbitan Isostearate, Disodium EDTA, Laminaria Ochroleuca Extract, Pectin, Butylene Glycol, Sucrose, Glyceryl Acrylate/Acrylic Acid Copolymer, Capryloyl Glycine, Sodium Hyaluronate, Red 4 (CI 14700). 01